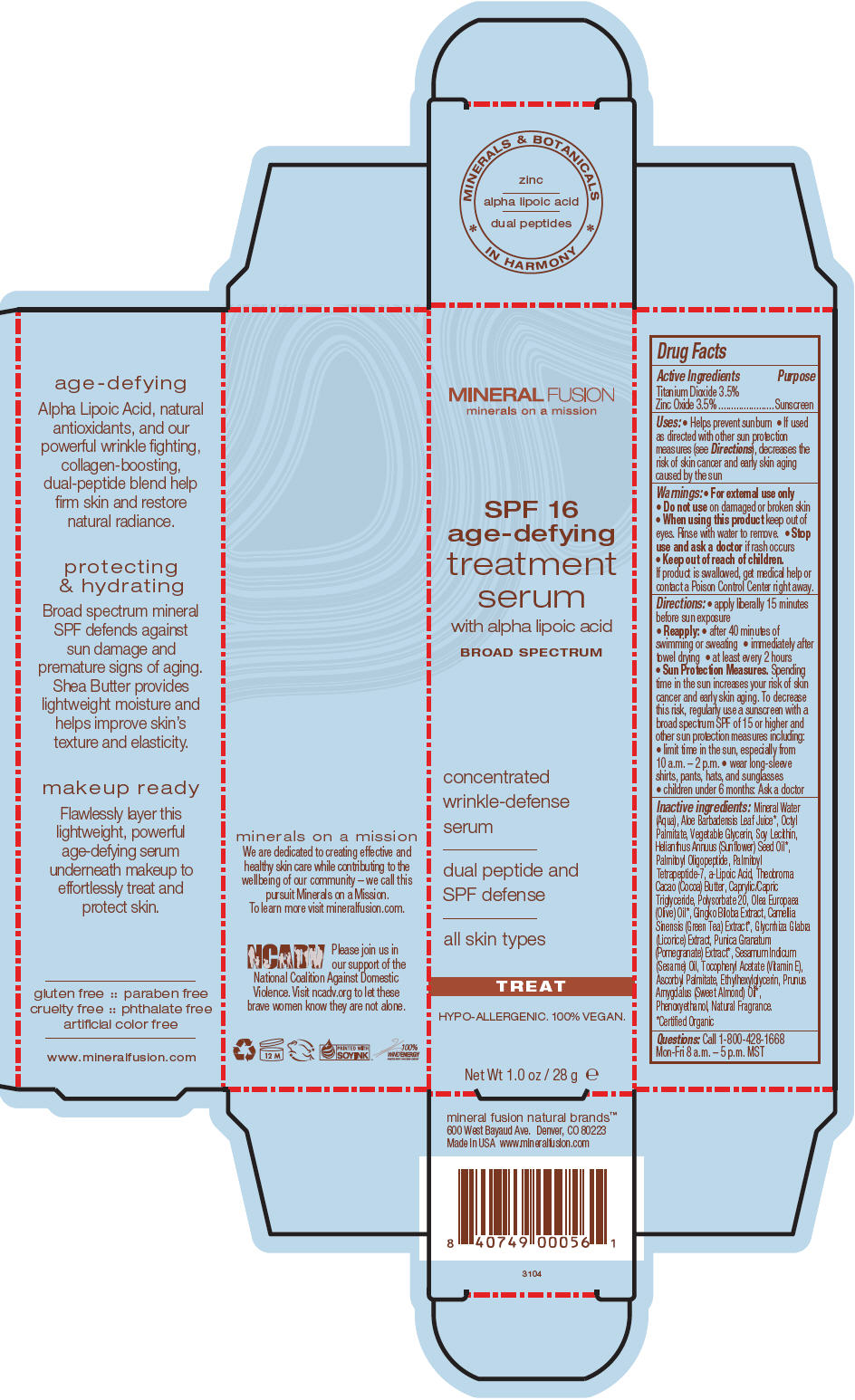 DRUG LABEL: SPF 16 AGE-DEFYING TREATMENT SERUM
NDC: 55789-3104 | Form: CREAM
Manufacturer: Mineral Fusion Natural Brands
Category: otc | Type: HUMAN OTC DRUG LABEL
Date: 20150821

ACTIVE INGREDIENTS: TITANIUM DIOXIDE 3.36 g/96 g; ZINC OXIDE 3.36 g/96 g
INACTIVE INGREDIENTS: WATER 67.2 g/96 g; ALOE VERA LEAF; ETHYLHEXYL PALMITATE; GLYCERIN; LECITHIN, SOYBEAN; SUNFLOWER OIL; PALMITOYL TETRAPEPTIDE-7; .ALPHA.-LIPOIC ACID; COCOA BUTTER; MEDIUM-CHAIN TRIGLYCERIDES; POLYSORBATE 20; OLIVE OIL; GINKGO; GREEN TEA LEAF; LICORICE; POMEGRANATE; SESAME OIL; TOCOPHEROL; ASCORBYL PALMITATE; ETHYLHEXYLGLYCERIN; ALMOND OIL; PHENOXYETHANOL

SPF 16 AGE-DEFYING TREATMENT SERUM

Drug Facts

Active Ingredients

Titanium Dioxide 3.5%
Zinc Oxide 3.5%

Purpose

Sunscreen

Uses

- Helps prevent sunburn
- If used as directed with other sun protection measures (see Directions), decreases the risk of skin cancer and early skin aging caused by the sun

Warnings

- For external use only

- Do not use on damaged or broken skin

- When using this product keep out of eyes. Rinse with water to remove.

- Stop use and ask a doctor if rash occurs

- Keep out of reach of children. If product is swallowed, get medical help or contact a Poison Control Center right away.

Directions

- apply liberally 15 minutes before sun exposure
- Reapply:
  - after 40 minutes of swimming or sweating
  - immediately after towel drying
  - at least every 2 hours
- Sun Protection Measures. Spending time in the sun increases your risk of skin cancer and early skin aging. To decrease this risk, regularly use a sunscreen with a broad spectrum SPF of 15 or higher and other sun protection measures including:
  - limit time in the sun, especially from 10 a.m. – 2 p.m.
  - wear long-sleeve shirts, pants, hats, and sunglasses
- children under 6 months: Ask a doctor

Inactive ingredients

Mineral Water (Aqua), Aloe Barbadensis Leaf Juice [Certified Organic] , Octyl Palmitate, Vegetable Glycerin, Soy Lecithin, Helianthus Annuus (Sunflower) Seed Oil, Palmitoyl Oligopeptide, Palmitoyl Tetrapeptide-7, a-Lipoic Acid, Theobroma Cacao (Cocoa) Butter, Caprylic/Capric Triglyceride, Polysorbate 20, Olea Europaea (Olive) Oil, Gingko Biloba Extract, Camellia Sinensis (Green Tea) Extract, Glycrrhiza Glabra (Licorice) Extract, Punica Granatum (Pomegranate) Extract, Sesamum Indicum (Sesame) Oil, Tocopheryl Acetate (Vitamin E), Ascorbyl Palmitate, Ethylhexylglycerin, Prunus Amygdalus (Sweet Almond) Oil, Phenoxyethanol, Natural Fragrance.

Questions

Call 1-800-428-1668 Mon-Fri 8 a.m. – 5 p.m. MST

PRINCIPAL DISPLAY PANEL - 28 g Tube Carton

MINERAL FUSION
minerals on a mission

SPF 16
age-defying
treatment
serum
with alpha lipoic acid

BROAD SPECTRUM

concentrated
wrinkle-defense
serum

dual peptide and
SPF defense

all skin types

TREAT

HYPO-ALLERGENIC. 100% VEGAN.

Net Wt 1.0 oz / 28 g e